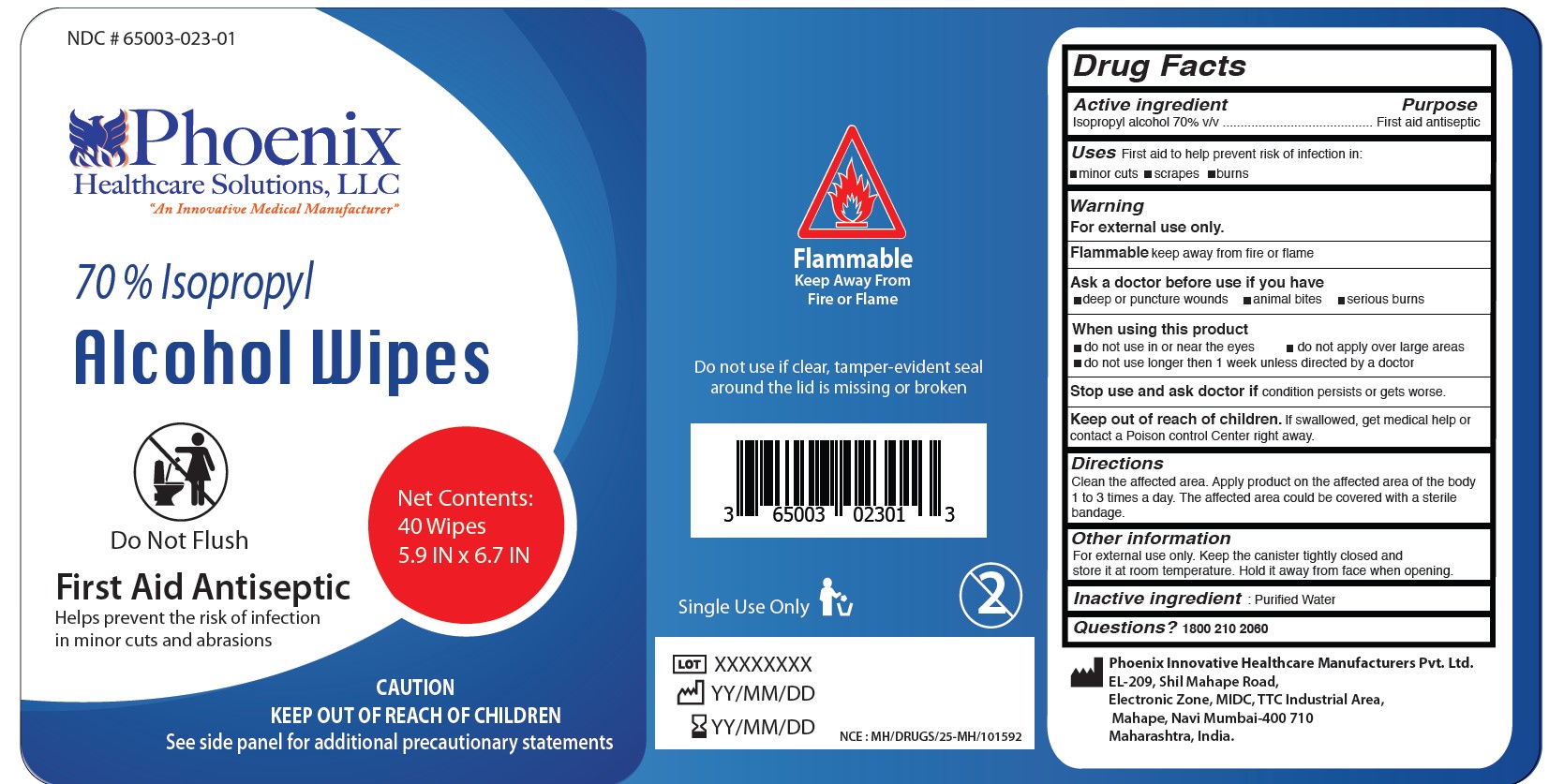 DRUG LABEL: Alcohol Wipes
NDC: 60913-038 | Form: CLOTH
Manufacturer: Phoenix Healthcare Solutions LLC
Category: otc | Type: HUMAN OTC DRUG LABEL
Date: 20251023

ACTIVE INGREDIENTS: ISOPROPYL ALCOHOL 70 mL/100 mL
INACTIVE INGREDIENTS: WATER

Phoenix Alcohol Wipes 40 ct

ACTIVE INGREDIENT

Isopropyl Alcohol 70%

PURPOSE

First aid Antiseptic

INDICATIONS AND USAGE

First aid to help prevent the risk of infection in minor cuts, scrapes or burns.

WARNINGS

For external use only

SAFE HANDLING WARNING

Flammable keep away from fire or flame

ASK DOCTOR

Deep or puncture wounds

animal bites

serious burns

Do not use in or near the eyes

Do not apply over large areas

Do not use longer than 1 week unless directed by doctor

Stop use and ask doctor if condition persists or get worse

KEEP OUT OF REACH OF CHILDREN

If swallowed, get medical help or contact a Poison control center right away

DOSAGE AND ADMINISTRATION

Clean the affected area

Apply product on the affected area of the body 1 to 3 times a day

The affected area could be covered with a sterile bandage

OTHER SAFETY INFORMATION

For external use only

Keep the canister tightly closedand store it at room temperature

Hold it away from face when opening

INACTIVE INGREDIENT

Purified water

QUESTIONS

18002102060